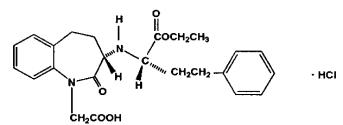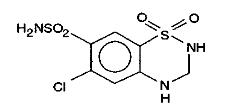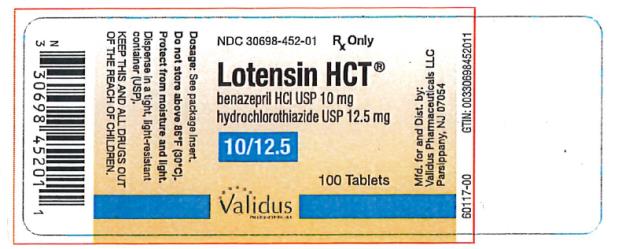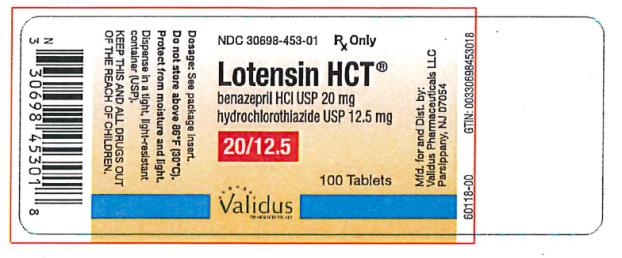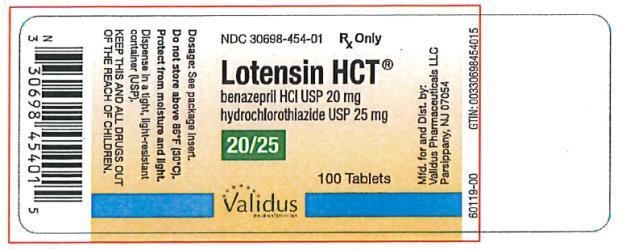 DRUG LABEL: Lotensin HCT
NDC: 30698-452 | Form: TABLET
Manufacturer: Validus Pharmaceuticals LLC
Category: prescription | Type: HUMAN PRESCRIPTION DRUG LABEL
Date: 20260224

ACTIVE INGREDIENTS: BENAZEPRIL HYDROCHLORIDE 10 mg/1 1; HYDROCHLOROTHIAZIDE 12.5 mg/1 1
INACTIVE INGREDIENTS: CELLULOSE, MICROCRYSTALLINE; CROSPOVIDONE; HYDROGENATED CASTOR OIL; FERRIC OXIDE RED; LACTOSE, UNSPECIFIED FORM; POLYETHYLENE GLYCOL, UNSPECIFIED; TALC; TITANIUM DIOXIDE

Lotensin HCT

Lotensin HCT®

(benazeprilhydrochloride USPandhydrochlorothiazide USP) Tablets

Combination Tablets

10 mg/12.5 mg
20 mg/12.5 mg
20 mg/25 mg

Rx Only

Prescribing Information

WARNING: FETAL TOXICITY

When pregnancy is detected, discontinue Lotensin HCT as soon as possible.

Drugs that act directly on the renin-angiotensin system can cause injury and death to the developing fetus (see WARNINGS: Fetal Toxicity).

DESCRIPTION

Benazepril hydrochloride USP is a white to off-white crystalline powder, soluble (>100 mg/mL) in water, in ethanol, and in methanol. Benazepril hydrochloride’s chemical name is 3-[[1-(ethoxycarbonyl)-3-phenyl-(1S)-propyl] amino]-2,3,4,5-tetrahydro-2-oxo-1 H-1-(3S)-benzazepine-1-acetic acid monohydrochloride; its structural formula is

Its empirical formula is C24H28N2O5·HCl, and its molecular weight is 460.96.

Benazeprilat, the active metabolite of benazepril, is a nonsulfhydryl angiotensin-converting enzyme inhibitor. Benazepril is converted to benazeprilat by hepatic cleavage of the ester group.

Hydrochlorothiazide USP is a white or practically white, practically odorless, crystalline powder. It is slightly soluble in water; freely soluble in sodium hydroxide solution, in n-butylamine, and in dimethylformamide; sparingly soluble in methanol; and insoluble in ether, in chloroform, and in dilute mineral acids. Hydrochlorothiazide’s chemical name is 6-chloro-3,4-dihydro-2 H-1,2,4- benzothiadiazine-7-sulfonamide 1,1-dioxide; its structural formula is

Its empirical formula is C7H8ClN3O4S2, and its molecular weight is 297.73. Hydrochlorothiazide is a thiazide diuretic.

Lotensin HCT is a combination of benazepril and hydrochlorothiazide USP. The tablets are formulated for oral administration with a combination of 10 or 20 mg of benazepril and 12.5 or 25 mg of hydrochlorothiazide USP. The inactive ingredients of the tablets are cellulose compounds, crospovidone, hydrogenated castor oil, iron oxides (10/12.5 mg, 20/12.5 mg, and 20/25 mg tablets), lactose, polyethylene glycol, talc, and titanium dioxide.

CLINICAL PHARMACOLOGY

Mechanism of Action

Benazepril and benazeprilat inhibit angiotensin-converting enzyme (ACE) in human subjects and in animals. ACE is a peptidyl dipeptidase that catalyzes the conversion of angiotensin I to the vasoconstrictor substance, angiotensin II. Angiotensin II also stimulates aldosterone secretion by the adrenal cortex.

Inhibition of ACE results in decreased plasma angiotensin II, which leads to decreased vasopressor activity and to decreased aldosterone secretion. The latter decrease may result in a small increase of serum potassium. Hypertensive patients treated with benazepril alone for up to 52 weeks had elevations of serum potassium of up to 0.2 mEq/L. Similar patients treated with benazepril and hydrochlorothiazide for up to 24 weeks had no consistent changes in their serum potassium (see PRECAUTIONS).

Removal of angiotensin II negative feedback on renin secretion leads to increased plasma renin activity. In animal studies, benazepril had no inhibitory effect on the vasopressor response to angiotensin II and did not interfere with the hemodynamic effects of the autonomic neurotransmitters acetylcholine, epinephrine, and norepinephrine.

ACE is identical to kininase, an enzyme that degrades bradykinin. Whether increased levels of bradykinin, a potent vasodepressor peptide, play a role in the therapeutic effects of Lotensin HCT remains to be elucidated.

While the mechanism through which benazepril lowers blood pressure is believed to be primarily suppression of the renin-angiotensin-aldosterone system, benazepril has an antihypertensive effect even in patients with low-renin hypertension.

Hydrochlorothiazide is a thiazide diuretic. Thiazides affect the renal tubular mechanisms of electrolyte reabsorption, directly increasing excretion of sodium and chloride in approximately equivalent amounts. Indirectly, the diuretic action of hydrochlorothiazide reduces plasma volume, with consequent increases in plasma renin activity, increases in aldosterone secretion, increases in urinary potassium loss, and decreases in serum potassium. The renin-aldosterone link is mediated by angiotensin, so coadministration of an ACE inhibitor tends to reverse the potassium loss associated with these diuretics.

The mechanism of the antihypertensive effect of thiazides is unknown.

Pharmacokinetics and Metabolism

Following oral administration of Lotensin HCT, peak plasma concentrations of benazepril are reached within 0.5 to 1.0 hour. As determined by urinary recovery, the extent of absorption is at least 37%. In fasting subjects, the rate and extent of absorption of benazepril and hydrochlorothiazide from Lotensin HCT are not different, respectively, from the rate and extent of absorption of benazepril and hydrochlorothiazide from immediate-release monotherapy formulations.

The estimated absolute bioavailability of hydrochlorothiazide after oral administration is about 70%. Peak plasma hydrochlorothiazide concentrations (Cmax) are reached within 2 to 5 hours after oral administration. Hydrochlorothiazide binds to albumin (40% to 70%) and distributes into erythrocytes.

The absorption of benazepril from Lotensin tablets is not influenced by the presence of food in the gastrointestinal tract. There is no clinically significant effect of food on the bioavailability of hydrochlorothiazide.

Cleavage of the ester group (primarily in the liver) converts benazepril to its active metabolite, benazeprilat. Peak plasma concentrations of benazeprilat are reached 1 to 2 hours after drug intake in the fasting state and 2 to 4 hours after drug intake in the nonfasting state. The serum protein binding of benazepril is about 96.7% and that of benazeprilat about 95.3%, as measured by equilibrium dialysis; on the basis of in vitrostudies, the degree of protein binding should be unaffected by age, hepatic dysfunction, or – over the concentration range of 0.24 to 23.6 µmol/L – concentration.

In studies of rats given^14C-benazepril, benazepril and its metabolites crossed the blood-brain barrier only to an extremely low extent. Multiple doses of benazepril did not result in accumulation in any tissue except the lung, where, as with other ACE inhibitors in similar studies, there was a slight increase in concentration due to slow elimination in that organ.

Benazepril is almost completely metabolized to benazeprilat, which has much greater ACE inhibitory activity than benazepril, and to the glucuronide conjugates of benazepril and benazeprilat. Only trace amounts of an administered dose of benazepril can be recovered unchanged in the urine; about 20% of the dose is excreted as benazeprilat, 4% as benazepril glucuronide, and 8% as benazeprilat glucuronide.

In patients with hepatic dysfunction due to cirrhosis, levels of benazeprilat are essentially unaltered. Similarly, the pharmacokinetics of benazepril and benazeprilat do not appear to be influenced by age.

The kinetics of benazepril are dose-proportional within the dosage range of 5 mg to 20 mg. Small deviations from dose proportionality were observed when the broader range of 2 mg to 80 mg was studied, possibly due to the saturable binding of the compound to ACE.

The effective half-life of accumulation of benazeprilat following multiple dosing of benazepril is 10 to11 hours. Thus, steady-state concentrations of benazeprilat should be reached after 2 or 3 doses of benazepril given once daily.

During chronic administration (28 days) of once-daily doses of benazepril between 5 mg and 20 mg, the kinetics did not change, and there was no significant accumulation. Accumulation ratios based on AUC and urinary recovery of benazeprilat were 1.19 and 1.27, respectively.

When dialysis was started 2 hours after ingestion of 10 mg of benazepril, approximately 6% of benazeprilat was removed in 4 hours of dialysis. The parent compound, benazepril, was not detected in the dialysate.

Benazepril and benazeprilat are cleared predominantly by renal excretion in healthy subjects with normal renal function. Nonrenal (i.e., biliary) excretion accounts for approximately 11% to 12% of benazeprilat excretion in healthy subjects. In patients with renal failure, biliary clearance may compensate to an extent for deficient renal clearance.

The disposition of benazepril and benazeprilat in patients with mild-to-moderate renal insufficiency (creatinine clearance > 30 mL/min) is similar to that in patients with normal renal function. In patients with creatinine clearance ≤ 30 mL/min, peak benazeprilat levels and the initial (alpha phase) half-life increase, and time to steady-state may be delayed (see DOSAGE AND ADMINISTRATION).

Following oral administration, plasma hydrochlorothiazide concentrations decline bi-exponentially, with a mean distribution half-life of about 2 hours and an elimination half-life of about 10 hours. About 70% of an orally administered dose of hydrochlorothiazide is eliminated in the urine as unchanged drug. In a study in individuals with impaired renal function, the mean elimination half-life of hydrochlorothiazide was increased to 2 fold in individuals with mild/moderate renal impairment (30 < CLcr < 90 mL/min) and 3 fold and severe renal impairment (≤ 30 mL/min), when compared to individuals with normal renal function (CLcr > 90 mL/min).

Pharmacodynamics

Benazepril

Single and multiple doses of 10 mg or more of benazepril cause inhibition of plasma ACE activity by at least 80% to 90% for at least 24 hours after dosing. For up to 4 hours after a 10 mg dose, pressor responses to exogenous angiotensin I were inhibited by 60% to 90%.

In normal human volunteers, single doses of benazepril caused an increase in renal blood flow but had no effect on glomerular filtration rate.

Hydrochlorothiazide

After oral administration of hydrochlorothiazide, diuresis begins within 2 hours, peaks in about 4 hours and lasts about 6 to 12 hours.

Drug Interactions

Lotensin HCT potentiates the antihypertensive action of other antihypertensive drugs (e.g., curare derivatives, guanethidine, methyldopa, beta-blockers, vasodilators, calcium channel blockers ACE inhibitors and ARBs and DRIs).

CLINICAL STUDIES

In single-dose studies, benazepril lowered blood pressure within 1 hour, with peak reductions achieved 2 to 4 hours after dosing. The antihypertensive effect of a single dose persisted for 24 hours. In multiple-dose studies, once-daily doses of 20 mg to 80 mg decreased seated pressure (systolic/diastolic) 24 hours after dosing by about 6-12/4-7 mm Hg. The reductions at trough are about 50% of those seen at peak.

Four dose-response studies of benazepril monotherapy using once-daily dosing were conducted in 470 mild-to-moderate hypertensive patients not using diuretics. The minimal effective once-daily dose of benazepril was 10 mg; further falls in blood pressure, especially at morning trough, were seen with higher doses in the studied dosing range (10 mg to 80 mg). In studies comparing the same daily dose of benazepril given as a single morning dose or as a twice-daily dose, blood pressure reductions at the time of morning trough blood levels were greater with the divided regimen.

The antihypertensive effects of benazepril were not appreciably different in patients receiving high- or low-sodium diets.

Benazepril-Hydrochlorothiazide

In 15 controlled clinical trials, 1453 healthy or hypertensive patients were exposed to benazepril and hydrochlorothiazide of which 459 were exposed for at least 6 months, 214 for at least 12 months and 25 for at least 24 months.

The combination of benazepril-hydrochlorothiazide resulted in mean placebo-adjusted decreases in sitting systolic and diastolic blood pressures of 10/6 mm Hg with 5/6.25 mg and 10/12.5 mg doses, and 20/10 mm Hg with 20/25 mg dose.

In clinical trials of benazepril/hydrochlorothiazideusing benazepril doses of 5/20 mg and hydrochlorothiazide doses of 6.25/25 mg, the antihypertensive effects were sustained for at least 24 hours, and they increased with increasing dose of either component. Although benazepril monotherapy is somewhat less effective in blacks than in nonblacks, the efficacy of combination therapy appears to be independent of race.

INDICATIONS AND USAGE

Lotensin HCT USP is indicated for the treatment of hypertension.

This fixed combination drug is not indicated for the initial therapy ofhypertension (see DOSAGE AND ADMINISTRATION).

CONTRAINDICATIONS

Lotensin HCT is contraindicated in patients who are anuric.

Lotensin HCT is also contraindicated in patients who are hypersensitive to benazepril, to any other ACE inhibitor, to hydrochlorothiazide, or to other sulfonamide-derived drugs. Hypersensitivity reactions are more likely to occur in patients with a history of allergy or bronchial asthma.

Lotensin HCT is also contraindicated in patients with a history of angioedema with or without previous ACE inhibitor treatment.

Lotensin HCT is contraindicated in combination with a neprilysin inhibitor (e.g., sacubitril). Do not administer Lotensin HCT within 36 hours of switching to or from sacubitril/valsartan, a neprilysin inhibitor (see WARNINGSand PRECAUTIONS).

Do not coadminister aliskiren with angiotensin receptor blockers, ACE inhibitors, including Lotensin HCT in patients with diabetes.

WARNINGS

Anaphylactoid and Possibly Related Reactions

Presumably because angiotensin-converting enzyme inhibitors affect the metabolism of eicosanoids and polypeptides, including endogenous bradykinin, patients receiving ACE inhibitors (including benazepril) may be subject to a variety of adverse reactions, some of them serious.

Head and Neck Angioedema:Angioedema of the face, extremities, lips, tongue, glottis, and larynx has been reported in patients treated with angiotensin-converting enzyme inhibitors. In U.S. clinical trials, symptoms consistent with angioedema were seen in none of the subjects who received placebo and in about 0.5% of the subjects who received benazepril. Angioedema associated with laryngeal edema can be fatal. If laryngeal stridor or angioedema of the face, tongue, or glottis occurs, treatment with Lotensin HCT should be discontinued and appropriate therapy instituted immediately. When involvement of the tongue, glottis, or larynx appears likely to cause airway obstruction, appropriate therapy, e.g., subcutaneous epinephrine injection 1:1000 (0.3- 0.5 mL) should be promptlyadministered (see PRECAUTIONSand ADVERSE REACTIONS).

Black patients receiving ACE inhibitors have been reported to have a higher incidence of angioedema compared to nonblacks.

Patients receiving coadministration of ACE inhibitor and mTOR (mammalian target of rapamycin) inhibitor (e.g., tesmsirolimus, sirolimus, everolimus) therapy or a neprilysin inhibitor may be at increased risk for angioedema (see PRECAUTIONS).

Intestinal Angioedema:Intestinal angioedema has been reported in patients treated with ACE inhibitors. These patients presented with abdominal pain (with or without nausea or vomiting); in some cases there was no prior history of facial angioedema and C-1 esterase levels were normal. The angioedema was diagnosed by procedures including abdominal CT scan or ultrasound, or at surgery, and symptoms resolved after stopping the ACE inhibitor. Intestinal angioedema should be included in the differential diagnosis of patients on ACE inhibitors presenting with abdominal pain.

Anaphylactoid Reactions During Desensitization:Two patients undergoing desensitizing treatment with hymenoptera venom while receiving ACE inhibitors sustained life-threatening anaphylactoid reactions. In the same patients, these reactions were avoided when ACE inhibitors were temporarily withheld, but they reappeared upon inadvertent rechallenge.

Anaphylactoid Reactions During Membrane Exposure:Anaphylactoid reactions have been reported in patients dialyzed with high-flux membranes and treated concomitantly with an ACE inhibitor. Anaphylactoid reactions have also been reported in patients undergoing low-density lipoprotein apheresis with dextran sulfate absorption.

Hypersensitivity reactions to hydrochlorothiazide are more likely in patients with allergy and asthma.

Hypotension

Lotensin HCT can cause symptomatic hypotension. Like other ACE inhibitors, benazepril has been only rarely associated with hypotension in uncomplicated hypertensive patients. Symptomatic hypotension is most likely to occur in patients who have been volume and/or salt depleted as a result of prolonged diuretic therapy, dietary salt restriction, dialysis, diarrhea, or vomiting. Volume and/or salt depletion should be corrected before initiating therapy with Lotensin HCT.

Lotensin HCT should be used cautiously in patients receiving concomitant therapy with other antihypertensives. The thiazide component of Lotensin HCT may potentiate the action of other antihypertensive drugs, especially ganglionic or peripheral adrenergic-blocking drugs. The antihypertensive effects of the thiazide component may also be enhanced in the postsympathectomy patient.

In patients with congestive heart failure, with or without associated renal insufficiency, ACE inhibitor therapy may cause excessive hypotension, which may be associated with oliguria, azotemia, and (rarely) with acute renal failure and death. In such patients, Lotensin HCT therapy should be started under close medical supervision; they should be followed closely for the first 2 weeks of treatment and whenever the dose of benazepril or diuretic is increased.

If hypotension occurs, the patient should be placed in a supine position, and, if necessary, treated with intravenous infusion of physiological saline. Lotensin HCT treatment usually can be continued following restoration of blood pressure and volume.

Impaired Renal Function

Monitor renal function periodically in patients treated with Lotensin HCT. Changes in renal function including acute renal failure can be caused by drugs that inhibit the renin-angiotensin system and by diuretics. Patients whose renal function may depend in part on the activity of the renin-angiotensin system (e.g., patients with renal artery stenosis, chronic kidney disease, severe congestive heart failure, or volume depletion) may be at particular risk of developing acute of acute renal failure on Lotensin HCT. Consider withholding or discontinuing therapy in patients who develop a clinically significant decrease in renal function on Lotensin HCT.

In a small study of hypertensive patients with unilateral or bilateral renal artery stenosis, treatment with benazepril was associated with increases in blood urea nitrogen and serum creatinine; these increases were reversible upon discontinuation of benazepril therapy, concomitant diuretic therapy, or both.

Neutropenia/Agranulocytosis

Another angiotensin-converting enzyme inhibitor, captopril, has been shown to cause agranulocytosis and bone marrow depression, rarely in uncomplicated patients (incidence probably less than once per 10,000 exposures) but more frequently (incidence possibly as great as once per 1000 exposures) in patients with renal impairment, especially those who also have collagen-vascular diseases such as systemic lupus erythematosus or scleroderma.

Available data from clinical trials of benazepril are insufficient to show that benazepril does not cause agranulocytosis at similar rates. Monitoring of white blood cell counts should be considered in patients with collagen-vascular disease, especially if the disease is associated with impaired renal function.

Fetal toxicity

Pregnancy

Use of drugs that act on the renin-angiotensin system during the second and third trimesters of pregnancy reduces fetal renal function and increases fetal and neonatal morbidity and death. Resulting oligohydramnios can be associated with fetal lung hypoplasia and skeletal deformations. Potential neonatal adverse effects include skull hypoplasia, anuria, hypotension, renal failure, and death. When pregnancy is detected, discontinue Lotensin HCT as soon as possible. These adverse outcomes are usually associated with use of these drugs in the second and third trimester of pregnancy. Most epidemiologic studies examining fetal abnormalities after exposure to antihypertensive use in the first trimester have not distinguished drugs affecting the renin-angiotensin system from other antihypertensive agents. Appropriate management of maternal hypertension during pregnancy is important to optimize outcomes for both mother and fetus.

In the unusual case that there is no appropriate alternative to therapy with drugs affecting the renin-angiotensin system for a particular patient, apprise the mother of the potential risk to the fetus. Perform serial ultrasound examinations to assess the intra-amniotic environment. If oligohydramnios is observed, discontinue Lotensin HCT, unless it is considered lifesaving for the mother. Fetal testing may be appropriate, based on the week of pregnancy. Patients and physicians should be aware, however, that oligohydramnios may not appear until after the fetus has sustained irreversible injury. Closely observe infants with histories of in uteroexposure to Lotensin HCT for hypotension, oliguria, and hyperkalemia (see PRECAUTIONS, Pediatric Use).

No teratogenic effects of Lotensin were seen in studies of pregnant rats, mice, and rabbits. On a mg/m^2basis, the doses used in these studies were 60 times (in rats), 9 times (in mice), and more than 0.8 times (in rabbits) the maximum recommended human dose (assuming a 50-kg woman). On a mg/kg basis these these multiples are 300 times (in rats), 90 times (in mice), and more than 3 times (in rabbits) the maximum recommended human dose. When hydrochlorothiazide was orally administered without benazepril to pregnant mice and rats during their respective periods of major organogenesis, at doses up to 3000 and 1000 mg/kg/day respectively, there was no evidence of harm to the fetus. Similarly, no teratogenic effects of benazepril were seen in studies of pregnant rats, mice, and rabbits; on a mg/kg basis, the doses used in these studies were 300 times (in rats), 90 times (in mice), and more than 3 times (in rabbits) the maximum recommended human dose.

Thiazides can cross the placenta, and concentrations reached in the umbilical vein approach those in the maternal plasma Hydrochlorothiazide, like other diuretics, can cause placental hypoperfusion. It accumulates in the amniotic fluid, with reported concentrations up to 19 times higher than in umbilical vein plasma. Use of thiazides during pregnancy is associated with a risk of fetal or neonatal jaundice or thrombocytopenia. Since they do not prevent or alter the course of EPH (Edema, Proteinuria, Hypertension) gestosis (pre-eclampsia), these drugs must not be used to treat hypertension in pregnant women. The use of hydrochlorothiazide for other indications (e.g., heart disease) in pregnancy should be avoided.

Hepatic Failure

Rarely, ACE inhibitors have been associated with a syndrome that starts with cholestatic jaundice and progresses to fulminant hepatic necrosis and (sometimes) death. The mechanism of this syndrome is not understood. Patients receiving ACE inhibitors who develop jaundice or marked elevations of hepatic enzymes should discontinue the ACE inhibitor and receive appropriate medical follow-up.

Systemic Lupus Erythematosus

Thiazide diuretics have been reported to cause exacerbation or activation of systemic lupus erythematosus.

Acute Myopia and Secondary Angle-Closure Glaucoma

Hydrochlorothiazide, a sulfonamide, can cause an idiosyncratic reaction, resulting in acute transient myopia and acute angle-closure glaucoma. Symptoms include acute onset of decreased visual acuity or ocular pain and typically occur within hours to weeks of drug initiation. Untreated acute angle-closure glaucoma can lead to permanent vision loss. The primary treatment is to discontinue hydrochlorothiazide as rapidly as possible. Prompt medical or surgical treatments may need to be considered if the intraocular pressure remains uncontrolled. Risk factors for developing acute angle-closure glaucoma may include a history of sulfonamide or penicillin allergy.

PRECAUTIONS

General

Serum Electrolyte Abnormalities

In clinical trials of Lotensin HCT, the average change in serum potassium was near zero in subjects who received 5/6.25 mg or 20/12.5 mg, but the average subject who received 10/12.5 mg or 20/25 mg experienced a mild reduction in serum potassium, similar to that experienced by the average subject receiving the same dose of hydrochlorothiazide monotherapy.

Hydrochlorothiazide can cause hypokalemia and hyponatremia. Hypomagnesemia can result in hypokalemia which appears difficult to treat despite potassium repletion. Drugs that inhibit the renin-angiotensin system can cause hyperkalemia. Monitor serum electrolytes periodically.

Metabolic Disturbances

Hydrochlorothiazide

Hydrochlorothiazide may alter glucose tolerance and raise serum levels of cholesterol and triglycerides.

Hydrochlorothiazide may raise the serum uric acid level due to reduced clearance of uric acid and may cause or exacerbate hyperuricemia and precipitate gout in susceptible patients.

Thiazides decrease urinary calcium excretion and may cause mild elevation of serum calcium. Avoid using Lotensin HCT in patients with hypercalcemia.

Cough: Presumably due to the inhibition of the degradation of endogenous bradykinin, persistent nonproductive cough has been reported with all ACE inhibitors, always resolving after discontinuation of therapy. ACE inhibitor-induced cough should be considered in the differential diagnosis of cough.

Surgery/Anesthesia:In patients undergoing surgery or during anesthesia with agents that produce hypotension, benazepril will block the angiotensin II formation that could otherwise occur secondary to compensatory renin release. Hypotension that occurs as a result of this mechanism can be corrected by volume expansion.

Information for Patients

Angioedema: Angioedema, including laryngeal edema, can occur at any time with treatment with ACE inhibitors. A patient receiving Lotensin HCT should be told to report immediately any signs or symptoms suggesting angioedema (swelling of face, eyes, lips, or tongue, or difficulty in breathing) and to take no more drugs until after consulting with the prescribing physician.

Pregnancy: Female patients of childbearing age should be told about the consequences of exposure to Lotensin HCT during pregnancy. Discuss treatment options with women planning to become pregnant. Patients should be asked to report pregnancies to their physicians as soon as possible.

Symptomatic Hypotension: A patient receiving Lotensin HCT should be cautioned that lightheadedness can occur, especially during the first days of therapy, and that it should be reported to the prescribing physician. The patient should be told that if syncope occurs, Lotensin HCT should be discontinued until the physician has been consulted.

All patients should be cautioned that inadequate fluid intake, excessive perspiration, diarrhea, or vomiting can lead to an excessive fall in blood pressure, with the same consequences of lightheadedness and possible syncope.

Hyperkalemia: A patient receiving Lotensin HCT should be told not to use potassium supplements or salt substitutes containing potassium without consulting the prescribing physician.

Neutropenia: Patients should be told to promptly report any indication of infection (e.g., sore throat, fever), which could be a sign of neutropenia.

Non-melanoma Skin Cancer: Instruct patients taking hydrochlorothiazide to protect skin from the sun and undergo regular skin cancer screening.

Laboratory Tests

The hydrochlorothiazide component of Lotensin HCT may decrease serum PBI levels without signs of thyroid disturbance.

Therapy with Lotensin HCT should be interrupted for a few days before carrying out tests of parathyroid function.

Drug Interactions

Neprilysin Inhibitors:

Patients taking concomitant neprilysin inhibitors may be at increased risk for angioedema.

Interactions Common for Both Benazepril and Hydrochlorothiazide

Potassium Supplements and Potassium-Sparing Diuretics:Concomitant use with Lotensin HCT may effect potassium levels. Monitor potassium periodically.

mTOR (mammalian target of rapamycin) inhibitors: Patients receiving coadministration of ACE inhibitor and mTOR inhibitor (e.g., temsirolimus, sirolimus, everolimus) therapy may be at increased risk for angioedema (see WARNINGS).

Lithium: Renal clearance of lithium is reduced by thiazides and increase the risk of lithium toxicity. Increased serum lithium levels and symptoms of lithium toxicity have been reported in patients receiving ACE inhibitors during therapy with lithium. Monitor lithium levels when used concomitantly with Lotensin HCT.

Dual Blockade of the Renin-Angiotensin System (RAS):Dual Blockade of the RAS with angiotensin receptor blockers, ACE inhibitors, or aliskiren is associated with increased risks of hypertension, hyperkalemia, and changes in renal function (including acute renal failure) compared to monotherapy. Most patients receiving the combination of two RAS inhibitors do not obtain any additional benefit compared to monotherapy. In general, avoid combined use of RAS inhibitors. Closely monitor blood pressure, renal function and electrolytes in patients on Lotensin HCT and other agents that affect the RAS.

Do not coadminister aliskiren with Lotensin HCT in patients with diabetes. Avoid use of aliskiren with Lotensin HCT in patients with renal impairment (GFR < 60 mL/min).

NSAIDs and Cox-2 selective agents: In patients who are elderly, volume-depleted (including those on diuretic therapy), or with compromised renal function, coadministration of NSAIDs, including selective COX-2 inhibitors, with ACE inhibitors, including benazepril, may result in deterioration of renal function, including possible acute renal failure. These effects are usually reversible. Monitor renal function periodically in patients receiving benazepril and NSAID therapy.

The antihypertensive effect of benazepril and hydrochlorothiazide may be attenuated by NSAIDs.

Benazepril

Benazepril has been used concomitantly with beta-adrenergic-blocking agents, calcium-blocking agents, cimetidine, diuretics, digoxin, hydralazine, and naproxen without evidence of clinically important adverse interactions. Other ACE inhibitors have had less than additive effects with beta-adrenergic blockers, presumably because drugs of both classes lower blood pressure by inhibiting parts of the renin-angiotensin system.

Interaction studies with warfarin and acenocoumarol have failed to identify any clinically important effects of benazepril on the serum concentrations or clinical effects of these anticoagulants.

Gold: Nitritoid reactions (symptoms include facial flushing, nausea, vomiting and hypotension)

have been reported rarely in patients on therapy with injectable gold (sodium aurothiomalate) and concomitant ACE inhibitor therapy.

Hydrochlorothiazide

Ion exchange resins:Stagger the dosage of hydrochlorothiazide and ion exchange resins such that hydrochlorothiazide is administered at least 4 hours before or 4 to 6 hours after the administration of resins. Single doses of either cholestyramine or colestipol resins bind the hydrochlorothiazide and reduce its absorption from the gastrointestinal tract by up to 85% and 43%, respectively.

Digitalis glycosides:Thiazide-induced hypokalemia or hypomagnesemia may predispose the patients to digoxin toxicity

Skeletal muscle relaxants:Possible increased responsiveness to muscle relaxants such as curare derivatives.

Antidiabetic agents: Dosage adjustment of antidiabetic drug may be required.

Antineoplastic agents(e.g., cyclophosphamide, methotrexate) :Concomitant use of thiazide diuretics may reduce renal excretion of cytotoxic agents and enhance their myelosuppressive effects.

Drugs that alter gastrointestinal motility: The bioavailability of thiazide-type diuretics may be increased by anticholinergic agents (e.g., atropine, biperiden), apparently due to a decrease in gastrointestinal motility and the stomach emptying rate. Conversely, pro-kinetic drugs may decrease the bioavailability of thiazide diuretics.

Cyclosporin: Concomitant treatment with diuretics may increase the risk of hyperuricaemia and gout-type complications.

Alcohol, barbiturates or narcotics:Concomitant administration of thiazide diuretics with alcohol, barbiturates, or narcotics may potentiate orthostatic hypotension.

Pressor amines:Hydrochlorothiazide may reduce the response to pressor amines such as noradrenaline but the clinical significance of this effect is not sufficient to preclude their use.

Non-clinical safety data

Carcinogenesis, Mutagenicity, Fertility

No evidence of carcinogenicity was found when benazeprilwas given to rats and mice for 104 weeks at doses up to 150 mg/kg/day. On a body-surface-area basis, this dose is 18 times (rats) and 9 times (mice) the maximum recommended human dose. No mutagenic activity was detected in the Ames test in bacteria (with or without metabolic activation), in an in vitrotest for forward mutations in cultured mammalian cells, or in a nucleus anomaly test. At doses of 50-500 mg/kg/day (6 to 61 times the maximum recommended dose on a body-surface-area basis), benazepril had no adverse effect on the reproductive performance of male and female rats.

Under the auspices of the National Toxicology Program, rats and mice received hydrochlorothiazidein their feed for 2 years, at doses up to 600 mg/kg/day in mice and up to 100 mg/kg/day in rats. These studies uncovered no evidence of a carcinogenic potential of hydrochlorothiazide in rats or female mice, but there was equivocal evidence of hepatocarcinogenicity in male mice.

Hydrochlorothiazide was not genotoxic in in vitroassays using strains TA 98, TA 100, TA 1535, TA 1537, and TA 1538 of Salmonella typhimurium(the Ames test); in the Chinese Hamster Ovary (CHO) test for chromosomal aberrations; or in in vivoassays using mouse germinal cell chromosomes, Chinese hamster bone marrow chromosomes, and the Drosophilasex-linked recessive lethal trait gene. Positive test results were obtained in the in vitroCHO Sister Chromatid Exchange (clastogenicity) test and in the Mouse Lymphoma Cell (mutagenicity) assays, using concentrations of hydrochlorothiazide of 43 to 1300 µg/mL. Positive test results were also obtained in the Aspergillusnidulansnondisjunction assay, using an unspecified concentration of hydrochlorothiazide.

Fertility

There are no human fertility data for hydrochlorothiazide. In animal studies, benazepril and hydrochlorothiazide alone or in combination had no effect on fertility and conception (see PRECAUTIONS, Non-Clinical Safety Data).

Use in Specific Populations

Nursing Mothers

Minimal amounts of unchanged benazepril and benazeprilat are excreted into the breast milk of lactating women treated with benazepril, so that a newborn child ingesting nothing but breast milk would receive less than 0.1% of the maternal doses of benazepril and benazeprilat. Thiazides, on the other hand, are definitely excreted into breast milk. Because of the potential for serious adverse reactions in nursing infants from hydrochlorothiazide and the unknown effects of benazepril in infants, a decision should be made whether to discontinue nursing or to discontinue Lotensin HCT, taking into account the importance of the drug to the mother.

Geriatric Use

Of the total number of patients who received Lotensin HCT in U.S. clinical studies of Lotensin HCT, 19% were 65 or older while about 1.5% were 75 or older. Overall differences in effectiveness or safety were not observed between these patients and younger patients.

A limited amount of data suggests that the systemic clearance of hydrochlorothiazide is reduced in both healthy and hypertensive elderly subjects compared to young healthy volunteers.

Pediatric Use

Neonates with a history ofin uteroexposure to Lotensin HCT:

If oliguria or hypotension occurs, direct attention toward support of blood pressure and renal perfusion. Exchange transfusions or dialysis may be required as a means of reversing hypotension and/or substituting for disordered renal function. Benazepril, which crosses the placenta, can theoretically be removed from the neonatal circulation by these means; there are occasional reports of benefit from these maneuvers with another ACE inhibitor, but experience is limited.

Safety and effectiveness in pediatric patients have not been established.

Renal Impairment

Safety and effectiveness of Lotensin HCT in patients with severe renal impairment (CrCL ≤ 30mL/min) have not been established. No dose adjustment is required in patients with mild (CrCL 60 to 90 mL/min) or moderate (CrCL 30 to 60 mL/min) renal impairment.

Hepatic Impairment

No adjustment of the initial dose is required for patients with mild to moderate hepatic impairment (see CLINICAL PHARMACOLOGY).

Hydrochlorothiazide

Minor alterations of fluid and electrolyte imbalance may precipitate hepatic coma in patients with impaired hepatic function or progressive liver disease.

ADVERSE REACTIONS

Lotensin HCT has been evaluated for safety in over 2500 patients with hypertension; over 500 of these patients were treated for at least 6 months, and over 200 were treated for more than 1 year.

The reported side effects were generally mild and transient, and there was no relationship between side effects and age, sex, race, or duration of therapy. Discontinuation of therapy due to side effects was required in approximately 7% of U.S. patients treated with Lotensin HCT and in 4% of patients treated with placebo.

The most common reasons for discontinuation of therapy with Lotensin HCT in U.S. studies were cough (1.0%; see PRECAUTIONS), “dizziness” (1.0%), headache (0.6%), and fatigue (0.6%).

The side effects considered possibly or probably related to study drug that occurred in U.S. placebo-controlled trials in more than 1% of patients treated with Lotensin HCT are shown in the table below.

Reactions Possibly or Probably Drug Related
Patients in U.S. Placebo-Controlled Studies
 | LOTENSIN HCT N = 665 |  | Placebo N = 235
 | N | % | N | %
“Dizziness” | 41 | 6.3 | 8 | 3.4
Fatigue | 34 | 5.2 | 6 | 2.6
Postural Dizziness | 23 | 3.5 | 1 | 0.4
Headache | 20 | 3.1 | 10 | 4.3
Cough | 14 | 2.1 | 3 | 1.3
Hypertonia | 10 | 1.5 | 3 | 1.3
Vertigo | 10 | 1.5 | 2 | 0.9
Nausea | 9 | 1.4 | 2 | 0.9
Impotence | 8 | 1.2 | 0 | 0.0
Somnolence | 8 | 1.2 | 1 | 0.4

Other side effects considered possibly or probably related to study drug that occurred in U.S. placebo-controlled trials in 0.3% to 1.0% of patients treated with Lotensin HCT were the following:

Cardiovascular:Palpitations, flushing.

Gastrointestinal: Vomiting, diarrhea, dyspepsia, anorexia, and constipation.

Neurologic and Psychiatric: Insomnia, nervousness, paresthesia, libido decrease, dry mouth, taste perversion, and tinnitus.

Dermatologic: Rash and sweating.

Other: Urinary frequency, arthralgia, myalgia, asthenia, and pain (including chest pain and abdominal pain).

Other adverse experiences reported in 0.3% or more of Lotensin HCT patients in U.S. controlled clinical trials, and rarer events seen in post-marketing experience, were the following; asterisked entries occurred in more than 1% of patients (in some, a causal relationship to Lotensin HCT is uncertain):

Cardiovascular: Syncope, peripheral vascular disorder, and tachycardia.

Body as a Whole: Infection, back pain*, flu syndrome*, fever, chills, and neck pain.

Dermatologic:Photosensitivity and pruritus.

Gastrointestinal: Gastroenteritis, flatulence, and tooth disorder.

Neurologic and Psychiatric: Hypesthesia, abnormal vision, abnormal dreams, and retinal disorder.

Respiratory: Upper respiratory infection*, epistaxis, bronchitis, rhinitis*, sinusitis*, and voice alteration.

Other: Conjunctivitis, arthritis, urinary tract infection, alopecia, and urinary frequency*.

Post-Marketing Experience

The following adverse reactions have been identified during post-approval use of either benazepril or hydrochlorothiazide. Because these reactions are reported voluntarily from a population of uncertain size, it is not always possible to estimate their frequency or establish a causal relationship to drug exposure:

Non-melanoma Skin Cancer:Hydrochlorothiazide is associated with an increased risk of non-melanoma skin cancer. In a study conducted in the Sentinel System, increased risk was predominantly for squamous cell carcinoma (SCC) and in white patients taking large cumulative doses. The increased risk for SCC in the overall population was approximately 1 additional case per 16,000 patients per year, and for white patients taking a cumulative dose of ≥50,000mg the risk increase was approximately 1 additional SCC case for every 6,700 patients per year.

BenazeprilStevens-Johnson syndrome, pancreatitis, hemolytic anemia, pemphigus, and thrombocytopenia, eosinophilic pneumonitis

Hydrochlorothiazide

Digestive: Pancreatitis, small bowel angioedema, jaundice (intrahepatic cholestatic), sialadenitis, vomiting, diarrhea, cramping, nausea, gastric irritation, constipation, and anorexia.

Neurologic: Vertigo, lightheadedness, transient blurred vision, headache, paresthesia, xanthopsia, weakness, and restlessness.

Musculoskeletal: Muscle spasm.

Hematologic: Aplastic anemia, agranulocytosis, leukopenia, neutropenia and thrombocytopenia.

Metabolic: Hyperglycemia, glycosuria, and hyperuricemia, pyrexia, asthenia, parathyroid gland changes with hypercalcemia and hypophosphatemia.

Hypersensitivity: Anaphylactoid reactions, necrotizing angiitis, respiratory distress (including pneumonitis and pulmonary edema), purpura, urticaria, rash, and photosensitivity.

Skin: Erythema multiforme including Stevens-Johnson syndrome, and exfoliative dermatitis including toxic epidermal necrolysis.

Clinical Laboratory Test Findings

Serum Electrolytes: see PRECAUTIONS.

Creatinine and BUN:Minor reversible increases in serum creatinine and BUN were observed in patients with essential hypertension treated with Lotensin HCT. Such increases occurred most frequently in patients with renal artery stenosis (see PRECAUTIONS).

To report SUSPECTED ADVERSE REACTIONS, contact Validus Pharmaceuticals LLC at 1-866-982-5438 or FDA at 1-800-FDA-1088 or www.fda.gov/medwatch.

OVERDOSAGE

No specific information is available on the treatment of overdosage with Lotensin HCT; treatment should be symptomatic and supportive. Therapy with Lotensin HCT should be discontinued, and the patient should be observed. Dehydration, electrolyte imbalance, and hypotension should be treated by established procedures.

Single oral doses of 1 g/kg of benazepril caused reduced activity in mice, and doses of 3 g/kg were associated with significant lethality. Reduction of activity in rats was not seen until they had received doses of 5 g/kg, and doses of 6 g/kg were not lethal. In single-dose studies of hydrochlorothiazide, most rats survived doses up to 2.75 g/kg.

Data from human overdoses of benazepril are scanty, but the most common manifestation of human benazepril overdosage is likely to be hypotension. In human hydrochlorothiazide overdose, the most common signs and symptoms observed have been those of dehydration and electrolyte depletion (hypokalemia, hypochloremia, hyponatremia). If digitalis has also been administered, hypokalemia may accentuate cardiac arrhythmias.

Laboratory determinations of serum levels of benazepril and its metabolites are not widely available, and such determinations have, in any event, no established role in the management of benazepril overdose.

No data are available to suggest physiological maneuvers (e.g., maneuvers to change the pH of the urine) that might accelerate elimination of benazepril and its metabolites. Benazeprilat is only slightly dialyzable, but dialysis might be considered in overdosed patients with severely impaired renal function (see WARNINGS).

Angiotensin II could presumably serve as a specific antagonist-antidote in the setting of benazepril overdose, but angiotensin II is essentially unavailable outside of scattered research facilities. Because the hypotensive effect of benazepril is achieved through vasodilation and effective hypovolemia, it is reasonable to treat benazepril overdose by infusion of normal saline solution.

DOSAGE AND ADMINISTRATION

Dose once daily. The dosage may then be increased after 2 to 3 weeks as needed to help achieve blood pressure goals. The maximum recommended dose is 20/25 mg.

Switch Therapy:A patient whose blood pressure is not adequately controlled with benazepril alone or with hydrochlorothiazide alone may be switched to combination therapy with Lotensin HCT. The usual recommended starting dose is 10/12.5 mg once daily to control blood pressure.

Replacement Therapy:The combination may be substituted for the titrated individual components.

HOW SUPPLIED

Lotensin HCT USP is available in tablets of three different strengths:

Benazepril HCl | Hydrochlorothiazide | Tablet Color
10 mg | 12.5 mg | light pink
20 mg | 12.5 mg | grayish violet
20 mg | 25 mg | red

Tablets of each strength are supplied in bottles that contain a desiccant and 100 tablets.

The National Drug Codes for the various packages are:

Dose | Bottle of 100 | Tablet Imprint
10/12.5 | NDC 30698-452-01 | 452
20/12.5 | NDC 30698-453-01 | 453
20/25 | NDC 30698-454-01 | 454

Tablets are oblong and scored, with “LOTENSIN HCT” on one side and appropriate number imprinted on the other side.

Storage: Do not store above 86°F (30°C). Protect from moisture and light. Dispense inatight, light-resistant container (USP).

Manufactured for and Distributed by:
Validus Pharmaceuticals LLC
Parsippany, NJ 07054
info@validuspharma.com
www.validuspharma.com
1-866-982-5438

© 2023 Validus Pharmaceuticals LLC

60024-06 March 2023

PRINCIPAL DISPLAY PANEL

10 mg benazepril/12.5 mg hydrochlorothiazide Tablet

NDC 30698-452-01

Lotensin HCT®
benazepril HCl USP 10 mg
hydrochlorothiazide USP 12.5 mg

10/12.5

100 Tablets

Rx Only

PRINCIPAL DISPLAY PANEL

20 mg benazepril/12.5 mg hydrochlorothiazide Tablet

NDC 30698-453-01

Lotensin HCT®20/12.5
benazepril HCl USP 20 mg
hydrochlorothiazide USP 12.5 mg

20/12.5

100 Tablets

Rx Only

PRINCIPAL DISPLAY PANEL

20 mg benazepril/25 mg hydrochlorothiazide Tablet

NDC 30698-454-01

Lotensin HCT®20/25
benazepril HCl USP 20 mg
hydrochlorothiazide USP 25 mg

20/25

100 Tablets

Rx Only